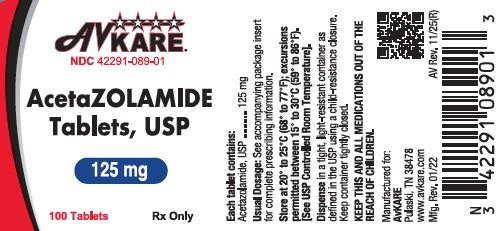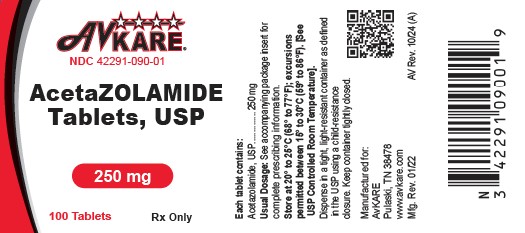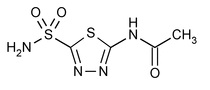 DRUG LABEL: acetazolamide
NDC: 42291-089 | Form: TABLET
Manufacturer: AvKARE
Category: prescription | Type: HUMAN PRESCRIPTION DRUG LABEL
Date: 20260224

ACTIVE INGREDIENTS: ACETAZOLAMIDE 125 mg/1 1
INACTIVE INGREDIENTS: LACTOSE MONOHYDRATE; MAGNESIUM STEARATE; CELLULOSE, MICROCRYSTALLINE; POVIDONE; STARCH, CORN; SODIUM LAURYL SULFATE; SODIUM STARCH GLYCOLATE TYPE A POTATO

Acetazolamide Tablets, USP

Rx Only DESCRIPTION

Acetazolamide, an inhibitor of the enzyme carbonic anhydrase is a white to faintly yellowish white crystalline, odorless powder, weakly acidic, very slightly soluble in water and slightly soluble in alcohol. The chemical name for acetazolamide is N-(5-Sulfamoyl-1,3,4-thiadiazol-2-yl)-acetamide and has the following chemical structure:

Molecular Weight: 222.25

Molecular Formula: C4H6N4 O3S2

Acetazolamide tablets, USP are available for oral administration each containing 125 mg and 250 mg of acetazolamide respectively. Additionally, they contain the following inactive ingredients: lactose monohydrate, magnesium stearate, microcrystalline cellulose, povidone, pregelatinized starch, sodium lauryl sulfate, and sodium starch glycolate.

CLINICAL PHARMACOLOGY

Acetazolamide is a potent carbonic anhydrase inhibitor, effective in the control of fluid secretion (e.g., some types of glaucoma), in the treatment of certain convulsive disorders (e.g., epilepsy) and in the promotion of diuresis in instances of abnormal fluid retention (e.g., cardiac edema).

Acetazolamide is not a mercurial diuretic. Rather, it is a nonbacteriostatic sulfonamide possessing a chemical structure and pharmacological activity distinctly different from the bacteriostatic sulfonamides.

Acetazolamide is an enzyme inhibitor that acts specifically on carbonic anhydrase, the enzyme that catalyzes the reversible reaction involving the hydration of carbon dioxide and the dehydration of carbonic acid. In the eye, this inhibitory action of acetazolamide decreases the secretion of aqueous humor and results in a drop in intraocular pressure, a reaction considered desirable in cases of glaucoma and even in certain nonglaucomatous conditions. Evidence seems to indicate that acetazolamide has utility as an adjuvant in the treatment of certain dysfunctions of the central nervous system (e.g., epilepsy). Inhibition of carbonic anhydrase in this area appears to retard abnormal, paroxysmal, excessive discharge from central nervous system neurons. The diuretic effect of acetazolamide is due to its action in the kidney on the reversible reaction involving hydration of carbon dioxide and dehydration of carbonic acid. The result is renal loss of HCO ion, which carries out sodium, water, and potassium. Alkalinization of the urine and promotion of diuresis are thus affected. Alteration in ammonia metabolism occurs due to increased reabsorption of ammonia by the renal tubules as a result of urinary alkalinization.

Placebo-controlled clinical trials have shown that prophylactic administration of acetazolamide at a dose of 250 mg every eight to 12 hours (or a 500 mg controlled-release capsule once daily) before and during rapid ascent to altitude results in fewer and/or less severe symptoms (such as headache, nausea, shortness of breath, dizziness, drowsiness, and fatigue) of acute mountain sickness (AMS). Pulmonary function (e.g., minute ventilation, expired vital capacity, and peak flow) is greater in the acetazolamide treated group, both in subjects with AMS and asymptomatic subjects. The acetazolamide treated climbers also had less difficulty in sleeping.

INDICATIONS AND USAGE

For adjunctive treatment of: edema due to congestive heart failure; drug-induced edema; centrencephalic epilepsies (petit mal, unlocalized seizures); chronic simple (open-angle) glaucoma, secondary glaucoma, and preoperatively in acute angle-closure glaucoma where delay of surgery is desired in order to lower intraocular pressure. Acetazolamide Tablets are also indicated for the prevention or amelioration of symptoms associated with acute mountain sickness in climbers attempting rapid ascent and in those who are very susceptible to acute mountain sickness despite gradual ascent.

CONTRAINDICATIONS

Acetazolamide therapy is contraindicated in situations in which sodium and/or potassium blood serum levels are depressed, in cases of marked kidney and liver disease or dysfunction, in suprarenal gland failure, and in hyperchloremic acidosis. It is contraindicated in patients with cirrhosis because of the risk of development of hepatic encephalopathy.

Long-term administration of acetazolamide is contraindicated in patients with chronic noncongestive angle-closure glaucoma since it may permit organic closure of the angle to occur while the worsening glaucoma is masked by lowered intraocular pressure.

WARNINGS

Fatalities have occurred, although rarely, due to severe reactions to sulfonamides including Stevens-Johnson syndrome, toxic epidermal necrolysis, fulminant hepatic necrosis, agranulocytosis, aplastic anemia, and other blood dyscrasias. Sensitizations may recur when a sulfonamide is readministered irrespective of the route of administration. If signs of hypersensitivity or other serious reactions occur, discontinue use of this drug.

Caution is advised for patients receiving concomitant highdose aspirin and acetazolamide, as anorexia, tachypnea, lethargy, coma and death have been reported.

PRECAUTIONS

General

Increasing the dose does not increase the diuresis and may increase the incidence of drowsiness and/or paresthesia. Increasing the dose often results in a decrease in diuresis. Under certain circumstances, however, very large doses have been given in conjunction with other diuretics in order to secure diuresis in complete refractory failure.

Information for Patients

Adverse reactions common to all sulfonamide derivatives may occur: anaphylaxis, fever, rash (including erythema multiforme, Stevens-Johnson syndrome, toxic epidermal necrolysis), crystalluria, renal calculus, bone marrow depression,
thrombocytopenic purpura, hemolytic anemia, leukopenia, pancytopenia and agranulocytosis. Precaution is advised for early detection of such reactions and the drug should be discontinued and appropriate therapy instituted.

In patients with pulmonary obstruction or emphysema where alveolar ventilation may be impaired, acetazolamide, which may precipitate or aggravate acidosis, should be used with caution.

Gradual ascent is desirable to try to avoid acute mountain sickness. If rapid ascent is undertaken and acetazolamide tablets are used, it should be noted that such use does not obviate the need for prompt descent if severe forms of high altitude sickness occur, i.e., high altitude pulmonary edema (HAPE) or high altitude cerebral edema.

Caution is advised for patients receiving concomitant highdose aspirin and acetazolamide, as anorexia, tachypnea, lethargy, coma and death have been reported (see WARNINGS).

Both increases and decreases in blood glucose levels have been described in patients treated with acetazolamide. This should be taken into consideration in patients with impaired glucose tolerance or diabetes mellitus.

Acetazolamide treatment may cause electrolyte imbalances, including hyponatremia and hypokalemia, as well as metabolic acidosis. Therefore, periodic monitoring of serum electrolytes is recommended. Particular caution is recommended in patients with conditions that are associated with, or predispose a patient to, electrolyte and acid/base imbalances, such as patients with impaired renal function (including elderly patients; see PRECAUTIONS, Geriatric Use), patients with diabetes mellitus, and patients with impaired alveolar ventilation.

Some adverse reactions to acetazolamide, such as drowsiness, fatigue, and myopia, may impair the ability to drive and operate machinery.

Laboratory Tests

To monitor for hematologic reactions common to all sulfonamides, it is recommended that a baseline CBC and platelet count be obtained on patients prior to initiating acetazolamide tablet therapy and at regular intervals during therapy. If significant changes occur, early discontinuance and institution of appropriate therapy are important. Periodic monitoring of serum electrolytes is recommended.

Drug Interactions
Aspirin - See WARNINGS.

Acetazolamide modifies phenytoin metabolism with increased serum levels of phenytoin. This may increase or enhance the occurrence of osteomalacia in some patients receiving chronic phenytoin therapy. Caution is advised in patients receiving chronic concomitant therapy.

By decreasing the gastrointestinal absorption of primidone, acetazolamide may decrease serum concentrations of primidone and its metabolites, with a consequent possible decrease in anticonvulsant effect. Caution is advised when beginning, discontinuing, or changing the dose of acetazolamide in patients receiving primidone.

Because of possible additive effects with other carbonic anhydrase inhibitors, concomitant use is not advisable. Acetazolamide may increase the effects of other folic acid antagonists.

Acetazolamide may increase or decrease blood glucose levels. Consideration should be taken in patients being treated with antidiabetic agents.

Acetazolamide decreases urinary excretion of amphetamine and may enhance the magnitude and duration of their effect. Acetazolamide reduces urinary excretion of quinidine and may enhance its effect.

Acetazolamide may prevent the urinary antiseptic effect of methenamine.

Acetazolamide increases lithium excretion and the lithium may be decreased.

Acetazolamide and sodium bicarbonate used concurrently increases the risk of renal calculus formation.

Acetazolamide may elevate cyclosporine levels.

Carcinogenesis, Mutagenesis, Impairment of Fertility

Long-term studies in animals to evaluate the carcinogenic potential of acetazolamide have not been conducted. In a bacterial mutagenicity assay, acetazolamide was not mutagenic when evaluated with and without metabolic activation.

The drug had no effect on fertility when administered in the diet to male and female rats at a daily intake of up to 4 times the recommended human dose of 1000 mg in a 50 kg individual.

Pregnancy

Teratogenic Effect

Acetazolamide, administered orally or parenterally, has been shown to be teratogenic (defects of the limbs) in mice, rats, hamsters and rabbits. There are no adequate and well-controlled studies in pregnant women. Acetazolamide should be used in pregnancy only if the potential benefit justifies the potential risk to the fetus.

Nursing Mothers

Because of the potential for serious adverse reaction in nursing infants from acetazolamide, a decision should be made whether to discontinue nursing or to discontinue the drug taking into account the importance of the drug to the mother.

Pediatric Use

The safety and effectiveness of acetazolamide in pediatric patients has not been established. Growth retardation has been reported in children receiving long-term therapy, believed secondary to chronic acidosis.

Geriatric Use

Metabolic acidosis, which can be severe, may occur in the elderly with reduced renal function.

Clinical studies of acetazolamide did not include sufficient numbers of subjects aged 65 and over to determine whether they respond differently from younger subjects. Other reported clinical experience has not identified differences in responses between the elderly and younger patients. In general, dose selection for an elderly patient should be cautious, usually starting at the low end of the dosing range, reflecting the greater frequency of decreased hepatic, renal, or cardiac function, and of concomitant disease or other drug therapy.

ADVERSE REACTIONS

Body as a whole: Headache, malaise, fatigue, fever, pain at injection site, flushing, growth retardation in children, flaccid paralysis, anaphylaxis

Digestive: Gastrointestinal disturbances such as nausea, vomiting, diarrhea

Hematological/Lymphatic: Blood dyscrasias such as aplastic anemia, agranulocytosis, leukopenia, thrombocytopenia, thrombocytopenic purpura, melena

Hepato-biliary disorders: Abnormal liver function, cholestatic jaundice, hepatic insufficiency, fulminant hepatic necrosis

Metabolic/Nutritional: Metabolic acidosis, electrolyte imbalance, including hypokalemia, hyponatremia, osteomalacia with long-term phenytoin therapy, loss of appetite, taste alteration, hyper/hypoglycemia

Nervous: Drowsiness, paraesthesia (including numbness and tingling of extremities and face), depression, excitement, ataxia, confusion, convulsions, dizziness

Skin: Allergic skin reactions including urticaria, photosensitivity, Stevens-Johnson syndrome, toxic epidermal necrolysis

Special senses: Hearing disturbances, tinnitus, transient myopia. Transient myopia is the result of forward movement of the ciliary body leading to a narrowing of the angle.

Urogenital: Crystalluria, increased risk of nephrolithiasis with long-term therapy, hematuria, glycosuria, renal failure, polyuria

To report SUSPECTED ADVERSE REACTIONS contact AvKARE at 1-855-361-3993; email drugsafety@avkare.com; or FDA at 1-800-FDA-1088 or www.fda.gov/medwatch.

OVERDOSAGE

No specific antidote is known. Treatment should be symptomatic and supportive.

Electrolyte imbalance, development of an acidotic state, and central nervous effects might be expected to occur. Serum electrolyte levels (particularly potassium) and blood pH levels should be monitored.

Supportive measures are required to restore electrolyte and pH balance. The acidotic state can usually be corrected by the administration of bicarbonate.

Despite its high intraerythrocytic distribution and plasma protein binding properties, acetazolamide may be dialyzable. This may be particularly important in the management of acetazolamide overdosage when complicated by the presence of renal failure.

DOSAGE AND ADMINISTRATION

Glaucoma

Acetazolamide should be used as an adjunct to the usual therapy. The dosage employed in the treatment of chronic simple (open-angle) glaucoma ranges from 250 mg to 1 g of acetazolamide per 24 hours, usually in divided doses for amounts over 250 mg. It has usually been found that a dosage in excess of 1 g per 24 hours does not produce an increased effect. In all cases, the dosage should be adjusted with careful individual attention both to symptomatology and ocular tension. Continuous supervision by a physician is advisable.

In treatment of secondary glaucoma and in the preoperative treatment of some cases of acute congestive (closed-angle) glaucoma, the preferred dosage is 250 mg every four hours, although some cases have responded to 250 mg twice daily on short-term therapy. In some acute cases, it may be more satisfactory to administer an initial dose of 500 mg followed by 125 or 250 mg every four hours depending on the individual case. A complementary effect has been noted when acetazolamide has been used in conjunction with miotics or mydriatics as the case demanded.

Epilepsy

It is not clearly known whether the beneficial effects observed in epilepsy are due to direct inhibition of carbonic anhydrase in the central nervous system or whether they are due to the slight degree of acidosis produced by the divided dosage. The best results to date have been seen in petit mal in children. Good results, however, have been seen in patients, both children and adult, in other types of seizures such as grand mal, mixed seizure patterns, myoclonic jerk patterns, etc. The suggested total daily dose is 8 to 30 mg per kg in divided doses. Although some patients respond to a low dose, the optimum range appears to be from 375 to 1000 mg daily. However, some investigators feel that daily doses in excess of 1 g do not produce any better results than a 1 g dose. When acetazolamide tablets are given in combination with other anticonvulsants, it is suggested that the starting dose should be 250 mg once daily in addition to the existing medications. This can be increased to levels as indicated above.

The change from other medications to acetazolamide should be gradual and in accordance with usual practice in epilepsy therapy.

Congestive Heart Failure

For diuresis in congestive heart failure, the starting dose is usually 250 to 375 mg once daily in the morning (5 mg/kg). If, after an initial response, the patient fails to continue to lose edema fluid, do not increase the dose but allow for kidney recovery by skipping medication for a day. Acetazolamide tablets yield best diuretic results when given on alternate days, or for two days alternating with a day of rest.

Failures in therapy may be due to overdosage or too frequent dosage. The use of acetazolamide does not eliminate the need for other therapy such as digitalis, bed rest, and salt restriction.

Drug-Induced Edema

Recommended dosage is 250 to 375 mg of acetazolamide once a day for one or two days, alternating with a day of rest.

Acute Mountain Sickness

Dosage is 500 mg to 1000 mg daily, in divided doses. In circumstances of rapid ascent, such as in rescue or military operations, the higher dose level of 1000 mg is recommended. It is preferable to initiate dosing 24 to 48 hours before ascent and to continue for 48 hours while at high altitude, or longer as necessary to control symptoms.

Note: The dosage recommendations for glaucoma and epilepsy differ considerably from those for congestive heart failure, since the first two conditions are not dependent upon carbonic anhydrase inhibition in the kidney which requires intermittent dosage if it is to recover from the inhibitory effect of the therapeutic agent.

Interference with Laboratory Tests
Sulfonamides may give false negative or decreased values for urinary phenolsulfonphthalein and phenol red elimination values for urinary protein, serum non-protein and for serum uric acid. Acetazolamide may produce an increased level of crystals in the urine.

Acetazolamide interferes with the HPLC method of assay for theophylline. Interference with the theophylline assay by acetazolamide depends on the solvent used in the extraction; acetazolamide may not interfere with other assay methods for theophylline.

HOW SUPPLIED

Acetazolamide Tablets USP, 125 mg are available for oral administration as white to off white, round tablet, debossed HP 287 on one side and scored on other side. They are supplied as follows:

Bottles of 100 Tablets NDC 42291-089-01

Acetazolamide Tablets USP, 250 mg are available for oral administration as white to off white, round tablet, debossed HP 288 on one side and scored in quarters on other side. They are supplied as follows:

Bottles of 100 Tablets NDC 42291-090-01

Store at 20° to 25°C (68° to 77°F); excursions permitted between 15° to 30°C (59° to 86°F). [See USP Controlled Room Temperature].

Dispense in a tight, light-resistant container as defined in the USP using a child-resistant closure.

Keep container tightly closed.

KEEP THIS AND ALL MEDICATIONS OUT OF THE REACH OF CHILDREN.

Manufactured for:

AvKARE
Pulaski, TN 38478
Mfg. Rev. 06/22
AV Rev. 06/23 (M)